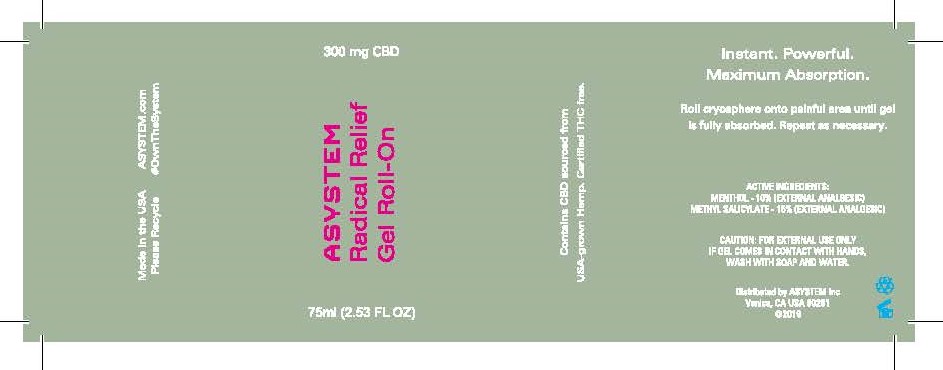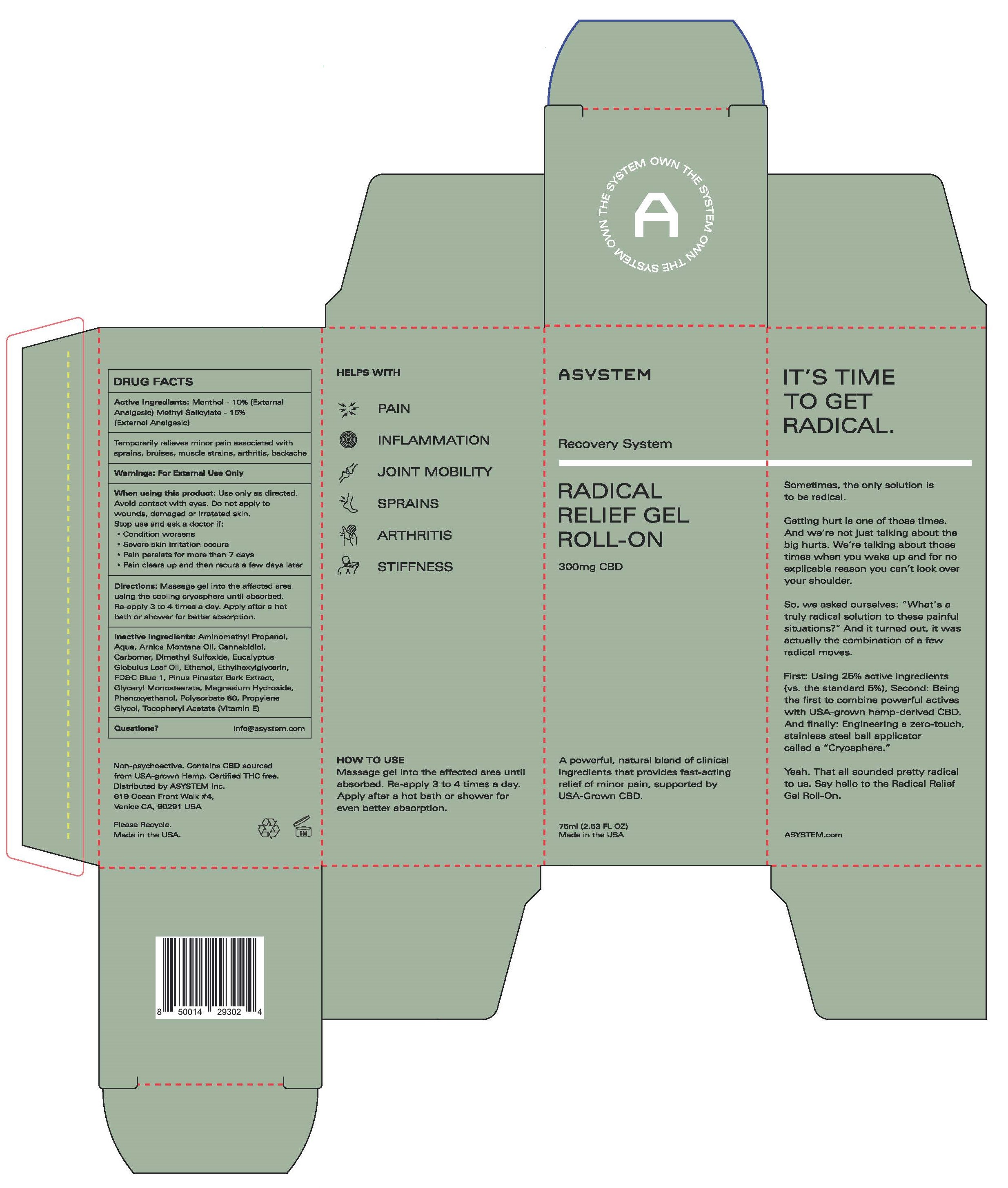 DRUG LABEL: ASYSTEM Radical Relief Gel Roll-On 300mg CBD
NDC: 52261-4901 | Form: GEL
Manufacturer: Cosco International, Inc.
Category: otc | Type: HUMAN OTC DRUG LABEL
Date: 20200319

ACTIVE INGREDIENTS: MENTHOL 0.10 kg/1 kg; METHYL SALICYLATE 0.15 kg/1 kg
INACTIVE INGREDIENTS: WATER; CARBOMER INTERPOLYMER TYPE A (ALLYL SUCROSE CROSSLINKED); MARITIME PINE; DIMETHYL SULFOXIDE; FD&C BLUE NO. 1; GLYCERYL MONOSTEARATE; POLYSORBATE 80; CANNABIDIOL; ARNICA MONTANA FLOWER; .ALPHA.-TOCOPHEROL ACETATE, DL-; GLYCERYL STEARATE/PEG-100 STEARATE; EUCALYPTUS OIL; PHENOXYETHANOL; ETHYLHEXYLGLYCERIN; MAGNESIUM HYDROXIDE; AMINOMETHYLPROPANOL

ASYSTEM Radical Relief Gel Roll-On 300mg CBD

DRUG FACTS

Menthol - 10% (External Analgesic)
Methyl Salicylate (NSAID) – 15% (External Analgesic)

PURPOSE

External Analgesic

INDICATIONS AND USAGE

Temporarily relieves minor pain associated with sprains, bruises, muscle strains, arthritis, backache

WARNINGS:

For External Use Only

Keep out of reach of children.
If swallowed, get medical help or contact a Poison Control Center immediately.

When using this product:

Use only as directed.

Avoid contact with eyes. Do not apply to wounds, damaged or irratated skin.

Stop usse and ask a doctor if:

- Condition worsens
- Severe skin irrataion occurs
- Pain persists for more than 7 days
- Pain ckears up and then recurs a few days later

DOSAGE AND ADMINISTRATION

Directions: Massage gel into the affected area using the cooling cryoshere until absorbed.

Re-apply 3 to 4 times a day. Apply after a hot bath or shower for better absorption.

Inactive Ingredients:

Alpha Tocopheryl Acetate (Vitamin E), Aminomethylpropanol, Arnica Montana Oil, Cannabidiol, Carbomer, Dimethyl Sulfoxide, Ethylhexylglycerin, Eucalyptus Oil, FD&C Blue No. 1, Maritime Pine, Glyceryl Monostearate, Glyceryl Stearate/PEG-100 Stearate, Magnesium Hydroxide, Phenoxyethanol, Polysorbate 80, Water

Questions?

info@asystem.com